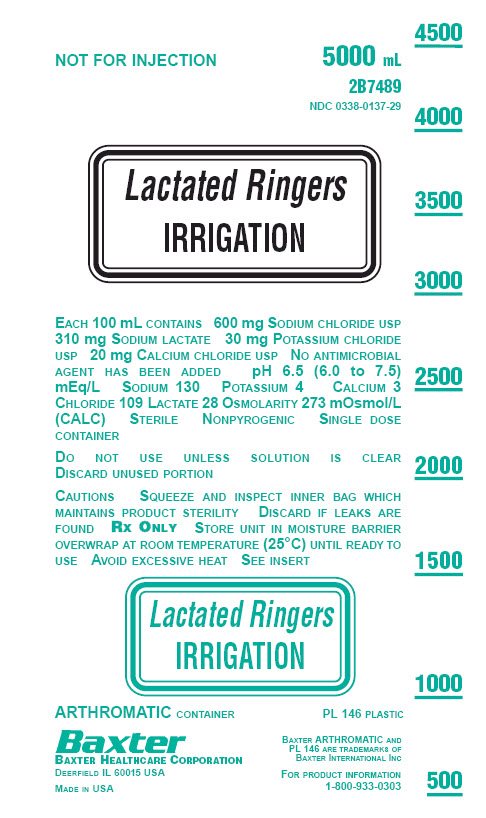 DRUG LABEL: Lactated Ringers
NDC: 0338-0137 | Form: IRRIGANT
Manufacturer: Baxter Healthcare Company
Category: prescription | Type: HUMAN PRESCRIPTION DRUG LABEL
Date: 20180102

ACTIVE INGREDIENTS: SODIUM CHLORIDE 6 g/1000 mL; SODIUM LACTATE 3.1 g/1000 mL; POTASSIUM CHLORIDE 300 mg/1000 mL; CALCIUM CHLORIDE 200 mg/1000 mL
INACTIVE INGREDIENTS: WATER

Lactated Ringer’s Irrigation
in ARTHROMATIC Plastic Container

DESCRIPTION

Lactated Ringer’s Irrigation is a sterile, nonpyrogenic, isotonic solution in a single dose ARTHROMATIC plastic container for use as an arthroscopic irrigating solution. Each liter contains 6.0 g Sodium Chloride, USP, (NaCl), 3.1 g Sodium Lactate (C3H5NaO3), 300 mg Potassium Chloride, USP, (KCl), and 200 mg Calcium Chloride, USP, (CaCl2•2H2O). pH 6.5 (6.0 to 7.5). Milliequivalents per liter: Sodium - 130, Potassium - 4, Calcium - 3, Chloride - 109, Lactate - 28. Osmolarity 273 mOsmol/L (calc.). No antimicrobial agent has been added.

The ARTHROMATIC plastic container is fabricated from a specially formulated polyvinyl chloride (PL 146 Plastic). The amount of water that can permeate from inside the container into the overwrap is insufficient to affect the solution significantly. Solutions in contact with the plastic container can leach out certain of its chemical components in very small amounts within the expiration period, e.g., di-2-ethylhexylphthalate (DEHP), up to 5 parts per million. However, the safety of the plastic has been confirmed in tests in animals according to USP biological tests for plastic containers as well as by tissue culture toxicity studies.

CLINICAL PHARMACOLOGY

Lactated Ringer’s Irrigation is useful as an irrigating fluid for body joints because it approximates the electrolyte composition of synovial fluid, and provides a transparent fluid medium with optical properties suitable for good visualization of the interior joint surface during endoscopic examination. During arthroscopic surgical procedures, the solution acts as a lavage for removing blood, tissue fragments, and bone fragments.

INDICATIONS AND USAGE

Lactated Ringer’s Irrigation is indicated for use as an arthroscopic irrigating fluid with endoscopic instruments during arthroscopic procedures requiring distension and irrigation of the knee, shoulder, elbow, or other bone joints.

CONTRAINDICATIONS

Lactated Ringer’s Irrigation is contraindicated in patients with a known hypersensitivity to Sodium Lactate.

WARNINGS

Absorption of large volume of irrigation fluids through a perforation or open wound may result in circulatory overload, cardiac failure, or electrolyte disturbances and acid-base imbalance.

Patients and fluid balance should be monitored accordingly. If absorption of clinically relevant amounts of fluid is suspected, the fluid administration should be interrupted, and the patient evaluated for possible adverse consequences.

Particularly close monitoring is required in patients with:

- Severely impaired renal function
- Impaired cardiac function, or
- Clinical states in which there is edema with sodium retention as a fluid overload syndrome may develop in these patients following absorption of even small quantities of irrigation fluid.

Appropriate therapy should be initiated, as indicated.

Lactated Ringer’s Irrigation must not be used when types of electrocautery are used that are not safe and effective when performed in the presence of electrolyte solutions.

Excessive volume or pressure during irrigation may cause excessive fluid absorption, undue distention of cavities, and/or disruption of tissue.

PRECAUTIONS

The container must not be vented.

Vented administration sets with the vent in the open position should not be used with flexible plastic containers. Use of a vented administration set with the vent in the open position could result in air embolism.

Pressurizing solutions contained in flexible plastic containers to increase flow rates can result in air embolism if the residual air in the container is not fully evacuated prior to administration.

Do not connect flexible plastic containers in series in order to avoid air embolism due to possible residual air contained in the primary container.

Drug Interactions

If clinically relevant amounts of solution have been absorbed, potential interactions with other agents must be considered, such as:

Patients treated with drugs that may increase the risk of sodium and fluid retention, such as corticosteroids and carbenoxolone, may have an increased risk of sodium and fluid retention.

Due to the alkalinizing action of lactate (formation of bicarbonate), Lactated Ringer’s Irrigation may interfere with the elimination of drugs for which renal elimination is pH dependent:

- Renal clearance of acidic drugs such as salicylates, barbiturates, and lithium may be increased.
- Renal clearance of alkaline drugs, such as sympathomimetics (e.g., ephedrine, pseudoephedrine), dextroamphetamine (dexamphetamine) sulfate, and fenfluramine (phenfluramine) hydrochloride may be decreased.

The risk of hyperkalemia is increased in patients treated with agents or products that can cause hyperkalemia or increase the risk of hyperkalemia, such as potassium-sparing diuretics (amiloride, spironolactone, triameterene), with ACE inhibitors, angiotensin II receptor antagonists, or the immunosuppressants tacrolimus and cyclosporine.

Administration of potassium in patients treated with such medications can produce severe and potentially fatal hyperkalemia, particularly in patients with severe renal insufficiency.

Absorption of calcium-containing solutions may increase the effects of digitalis and lead to serious or fatal cardiac arrhythmia.

In patients treated with thiazide diuretics or vitamin D, the risk of hypercalcemia is increased.

Pregnancy

Teratogenic Effects

Animal reproduction studies have not been conducted with Lactated Ringer’s Irrigation. It is also not known whether Lactated Ringer’s Irrigation can cause fetal harm when administered to a pregnant woman or can affect reproduction capacity. Lactated Ringer’s Irrigation should be given to a pregnant woman only if clearly needed.

Nursing Mothers

There is no adequate data from the use of Lactated Ringer’s Irrigation in lactating women. Physicians should carefully consider the potential risks and benefits for each specific patient before prescribing Lactated Ringer’s Irrigation.

Pediatric Use

Safety and effectiveness in pediatric patients have not been established by adequate and well-controlled trials.

Geriatric Use

When selecting the type of irrigation solution and the volume, duration of irrigation, and pressure for a geriatric patient, consider that geriatric patients are more likely to have cardiac, renal, hepatic, and other diseases or concomitant drug therapy.

ADVERSE REACTIONS

Post-Marketing Adverse Reactions

No adverse reactions were identified in Baxter’s Adverse Event Reporting System database with Lactated Ringer’s Irrigation.

Class Reactions

Adverse reactions reported with Lactated Ringer’s Irrigation (manufacturer unspecified) are: Fluid absorption manifested by Pulmonary edema, Edema, and Electrolyte disturbances.

Though not indicated for intravenous administration, absorption of irrigation fluid into tissue or vasculature through a perforation or open wound is possible. As a result, adverse reactions reported with Lactated Ringer’s solutions with and without Dextrose for intravenous administration may be applicable and include:

- Hypersensitivity reactions, including Anaphylactic/Anaphylactoid reactions, with the following manifestations: Angioedema, Chest pain, Chest discomfort, Decreased heart rate, Tachycardia, Blood pressure decreased, Respiratory distress, Bronchospasm, Dyspnea, Cough, Urticaria, Rash, Pruritus, Erythema, Flushing, Throat irritation, Paresthesias, Hypoesthesia oral, Dysgeusia, Nausea, Anxiety, Headache, Hyperkalemia
- Pyrexia

Overdose

In the event of clinically relevant absorption of irrigation fluid, the patients must be evaluated and corrective measures instituted as appropriate.

DOSAGE AND ADMINISTRATION

The volume and/or rate of solution needed will vary with the nature and duration of the arthroscopic procedure.

This solution, as it is packaged, is not intended for IV administration or injection.

The container must not be vented (See Precautions).

Parenteral drug products should be inspected visually for particulate matter and discoloration prior to administration whenever solution and container permit. Do not administer unless the solution is clear and the seal is intact. If particulate matter or discoloration is found, contact Baxter Customer Service

Aseptic technique should be used when applying this product.

The contents of an opened container should be used promptly to minimize the possibility of bacterial growth or pyrogen formation. Discard the unused portion of irrigating solution since no antimicrobial agent has been added.

When using Lactated Ringer’s Irrigation for pour irrigation, prevent contact of the fluid with the external surface of the container.

Lactated Ringer’s Irrigation is for single-patient use only.

Microwave heating of irrigation fluids is not recommended. If desired, Lactated Ringer’s Irrigation may be warmed in a water bath or oven to not more than 45° C while maintaining sterility. Lactated Ringer’s Irrigation that has been warmed must not be returned to storage.

Cetriaxone must not be mixed with calcium-containing solutions, including Lactated Ringer’s Irrigation.

Additives may be incompatible with Lactated Ringer’s Irrigation. Additives known or determined to be incompatible should not be used.

As with all parenteral solutions, compatibility of the additives with the solution must be assessed before addition, by checking for, for example, a possible color change and/or the appearance of precipitates, insoluble complexes, or crystals. Before adding a substance or medication, verify that it is soluble and/or stable in water and that the pH range of Lactated Ringer’s Irrigation is appropriate.

The instructions for use of the medication to be added and other relevant literature must be consulted.

When making additions to Lactated Ringer’s Irrigation, aseptic technique must be used. Mix the solution thoroughly when additives have been introduced. Do not store solutions containing additives.

HOW SUPPLIED

Lactated Ringer’s Irrigation in ARTHROMATIC Plastic Container is available as follows:

2B7487 | 3000 mL | NDC 0338-0137-27
2B7489 | 5000 mL | NDC 0338-0137-29

Exposure of pharmaceutical products to heat should be minimized. Avoid excessive heat. It is recommended the product be stored at room temperature (25° C); brief exposure up to 40° C does not adversely affect the product.

DIRECTIONS FOR USE

Tear overwrap down side at slit and remove solution container. Visually inspect the container. If the outlet port protector is damaged, detached, or not present, discard container as solution path sterility may be impaired. Some opacity of the plastic due to moisture absorption during the sterilization process may be observed. This is normal and does not affect the solution quality or safety. The opacity will diminish gradually. Check for minute leaks by squeezing bag firmly. If leaks are found, discard solution as sterility may be impaired.

Use Aseptic Technique.

1. Suspend container using hanger hole.
2. Remove protector from outlet port.
3. Attach irrigation set. Refer to complete directions accompanying set.

Baxter Healthcare Corporation
Deerfield, IL 60015 USA

Printed in USA

07-19-00-0210 Rev. January 2018

Baxter and Arthromatic are trademarks of Baxter International Inc.

PACKAGE LABEL - PRINCIPAL DISPLAY PANEL

Container Label

NOT FOR INJECTION

5000 mL

2B7489

NDC 0338-0137-29

Lactated Ringers

IRRIGATION

EACH 100 mL CONTAINS 600 mg SODIUM CHLORIDE USP
310 mg SODIUM LACTATE 30 mg POTASSIUM CHLORIDE
USP 20 mg CALCIUM CHLORIDE USP NO ANTIMICROBIAL
AGENT HAS BEEN ADDED pH 6.5 (6.0 to 7.5)
mEq/L SODIUM 130 POTASSIUM 4 CALCIUM 3
CHLORIDE 109 LACTATE 28 OSMOLARITY 273 mOsmol/L
(CALC) STERILE NONPYROGENIC SINGLE DOSE
CONTAINER

DO NOT USE UNLESS SOLUTION IS CLEAR
DISCARD UNUSED PORTION

CAUTIONS SQUEEZE AND INSPECT INNER BAG WHICH

MAINTAINS PRODUCT STERILITY DISCARD IF LEAKS ARE
FOUND RX ONLY STORE UNIT IN MOISTURE BARRIER
OVERWRAP AT ROOM TEMPERATURE (25°C) UNTIL READY TO
USE AVOID EXCESSIVE HEAT SEE INSERT

Lactated Ringers

IRRIGATION

ARTHROMATIC CONTAINER

PL 146 PLASTIC

Baxter
BAXTER HEALTHCARE CORPORATION
DEERFIELD IL 60015 USA

MADE IN USA

BAXTER ARTHROMATIC AND
PL 146 ARE TRADEMARKS OF
BAXTER INTERNATIONAL INC

FOR PRODUCT INFORMATION
1-800-933-0303